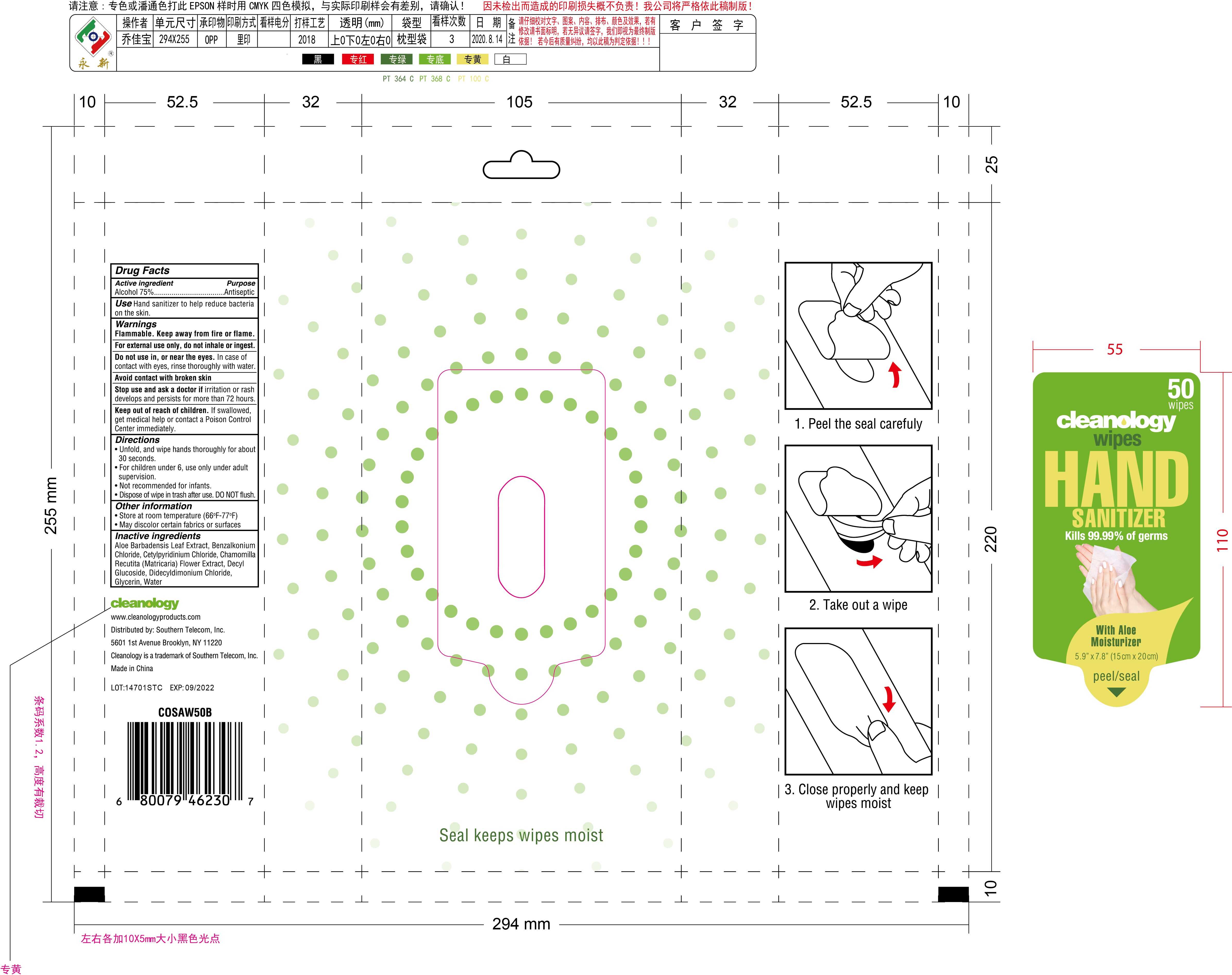 DRUG LABEL: sanitizing wipes
NDC: 42003-201 | Form: CLOTH
Manufacturer: Zhejiang Jiayan Daily Commodity Co., Ltd
Category: otc | Type: HUMAN OTC DRUG LABEL
Date: 20220225

ACTIVE INGREDIENTS: ALCOHOL 75 mL/100 1
INACTIVE INGREDIENTS: BENZALKONIUM CHLORIDE; CHAMOMILE; DECYL GLUCOSIDE; GLYCERIN; ALOE VERA LEAF; WATER; CETYLPYRIDINIUM CHLORIDE; DIDECYLDIMONIUM CHLORIDE

42003-201
sanitizing wipes

Active Ingredient(s)

Alcohol 75%

Purpose

Antiseptic

Use

Hand sanitizer to help reduce bacteria on the skin.

Warnings

Flammable. Keep away from fire or flame.

For external use only, do not inhale or ingest.

Do not use in, or near the eyes. In case of contact with eyes, rinse thoroughly with water.
Avoid contact with broken skin

Stop use and ask a doctor if irritation or rash develops and persists for more than 72 hours.

Keep out of reach of children. If swallowed, get medical help or contact a Poison Control Center immediately.

Do not use in, or near the eyes. In case of contact with eyes, rinse thoroughly with water.
Avoid contact with broken skin

Stop use and ask a doctor if irritation or rash develops and persists for more than 72 hours.

Keep out of reach of children. If swallowed, get medical help or contact a Poison Control Center immediately.

Stop use and ask a doctor if irritation or rash develops and persists for more than 72 hours.

Keep out of reach of children. If swallowed, get medical help or contact a Poison Control Center immediately.

Directions

Unfold, and wipe hands thoroughly for about 30 seconds.
For children under 6, use only under adult supervson.
Not recommended for infants.
Dispose of wipe in trash after use. DO NOT flush.

Other information

Store at room temperature (66°F-77°F)
May discolor certain fabrics or surfaces

Inactive ingredients

Aloe Barbadensis Leaf Extract, Benzalkonium Chloride, Cetylpyridinium Chloride, Chamomilla Recutita (Matricaria) Fllower Extract, Decyl Glucoside, Didecyldimonium Chloride, Glycerin, Water